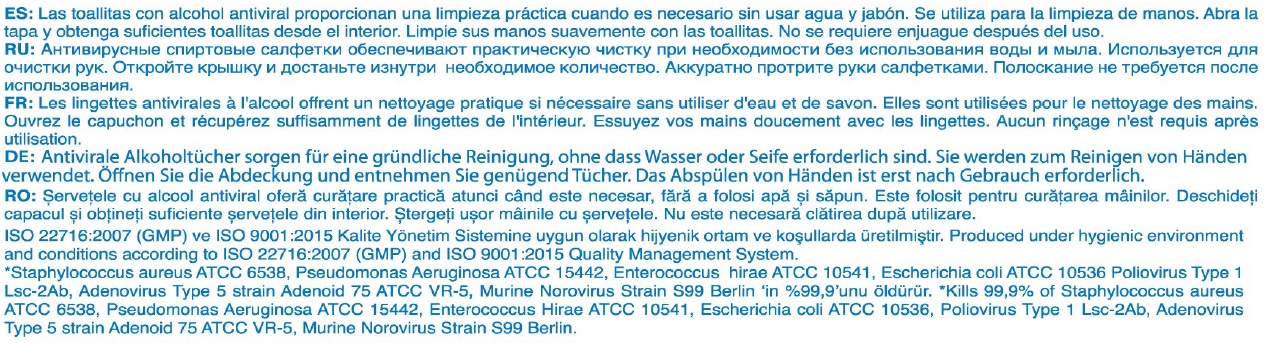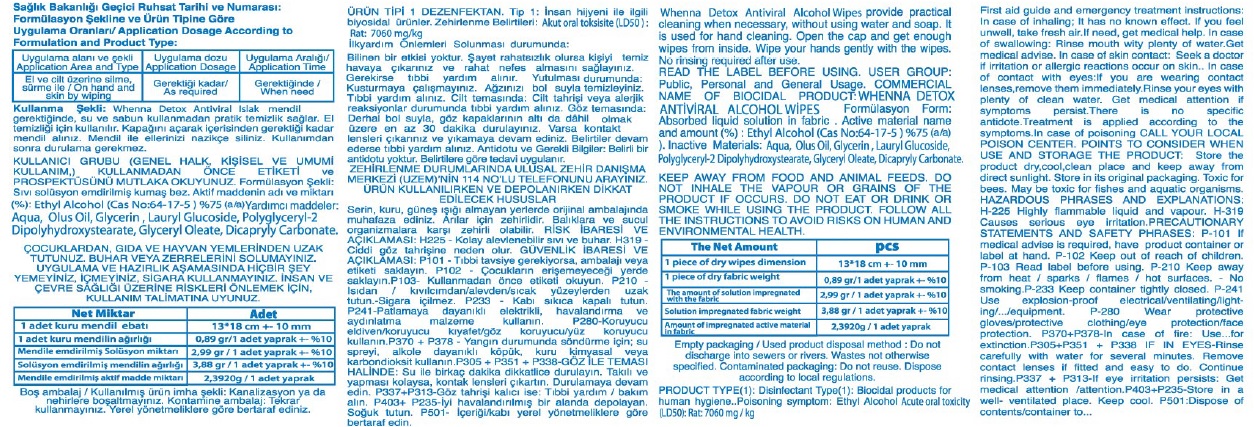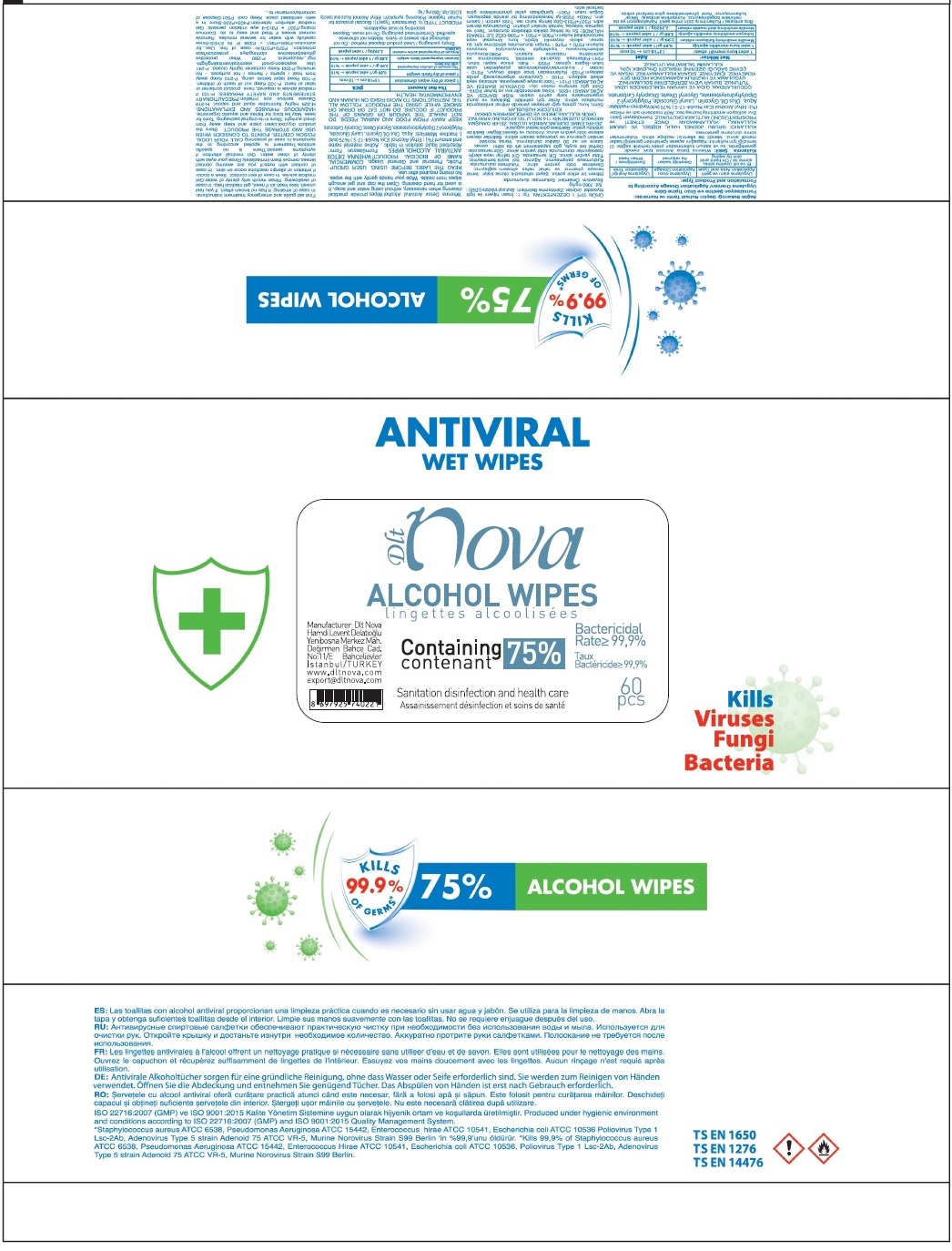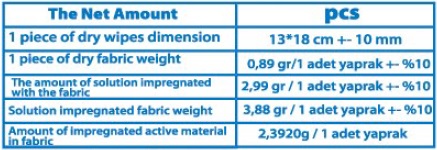 DRUG LABEL: DLT NOVA
NDC: 79475-101 | Form: CLOTH
Manufacturer: HAMDI LEVENT DELATIOGLU DLT NOVA DIS TICARET
Category: otc | Type: HUMAN OTC DRUG LABEL
Date: 20200717

ACTIVE INGREDIENTS: ALCOHOL 75 g/100 g
INACTIVE INGREDIENTS: WATER; CORN OIL; GLYCERIN; LAURYL GLUCOSIDE; POLYGLYCERYL-2 DIPOLYHYDROXYSTEARATE; GLYCERYL OLEATE; DICAPRYLYL CARBONATE

Dlt nova ALCOHOL WIPES

Active material name and amount (%)

Ethyl Alcohol %75

Purpose

Antiseptic

Uses

Whenna Detox Antiviral Alcohol Wipes provide practical cleaning when necessary, without using water and soap. It is used for hand cleaning.

Directions

Open the cap and get enough wipes from inside. Wipe your hands gently with the wipes. No rinsing requires after use.

Warnings

KEEP AWAY FROM FOOD AND ANIMAL FEEDS. DO NOT INHALE THE VAPOUR OR GRAINS OF THE PRODUCT IF OCCURS. DO NOT EAT OR DRINK OR SMOKE WHILE USING THE PRODUCT. FOLLOW ALL THE INSTRUCTIONS TO AVOID RISKS ON HUMAN AND ENVIRONMENTAL HEALTH.

First aid guide and emergency treatment instructions:

In case of inhaling; It has no known effect. If you feel unwell, take fresh air. If need, get medical help.

In case of swallowing: Rinse mouth with plenty of water. Get medical advise.

In case of skin contact: Seek a doctor if irritation or allergic reactions occur on skin.

In case of contact with eyes: If you are wearing contact lenses, remove them immediately. Rinse your eyes with plenty of clean water. Get medical attention if symptom persist. There is no specific antidote. Treatment is applied according to the symptoms.

In case of poisoning CALL YOUR LOCAL POISON CENTER.

Keep out of reach of children

POINTS TO CONSIDER WHEN USE AND STORAGE THE PRODUCT:

Store the product dry,cool,clean place and keep away from direct sunlight. Store in its original packaging

Inactive Materials:

Aqua, Olus Oil, Glycerin, Lauryl Glucoside, Polyglyceryl-2 Dipolyhydroxystearate, Glyceryl Oleate, Dicapryly Carbonate.

Containing 75%

Sanitation disinfection and healthcare

Bactericidal Rate≥ 99.9%

Manufacturer: Dlt Nova Hamdi Levent Delatioglu Yenibosna Merkez Mah.

Degirmen Bahce Cad.

No:11/E Bahcelievler

Istanbul/TURKEY

www.dltnova.com

export@dltnova.com

Kills

Viruses

Fungi

Bacteria

KILLS 9.99% OF GERMS*

75% ALCOHOL WIPES

Empty packaging/ Used product disposal method: Do not discharge into sewers or rivers. Wastes not otherwise specified. Contaminated packaging: Do not reuse. Dispose according to local regulations.

PRODUCT TYPE(1): Disinfectant Type(1): Biocidal products for human hygiene..Poisoning symptom: Ethyl Alcohol Acute oral toxicity

(LD50):Rat:7090mg/Kg

Toxic for bees. May be toxic for fishes and aquatic organisms.